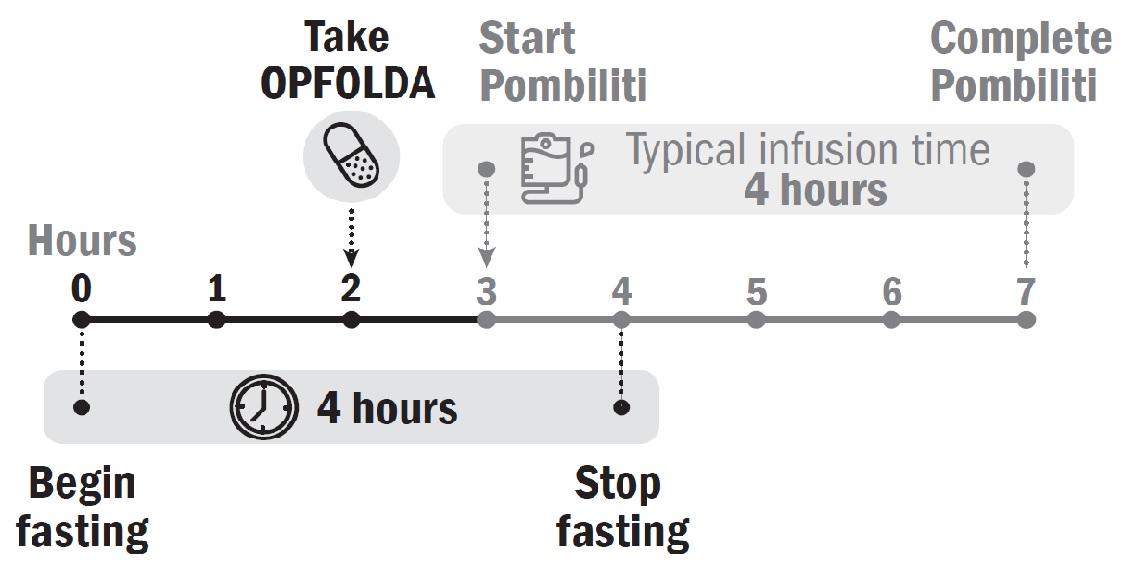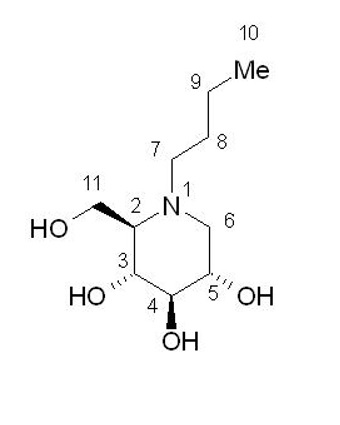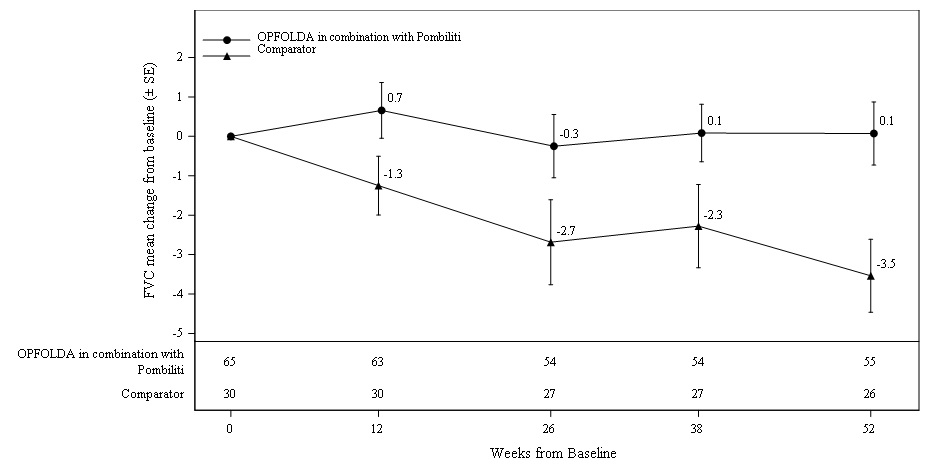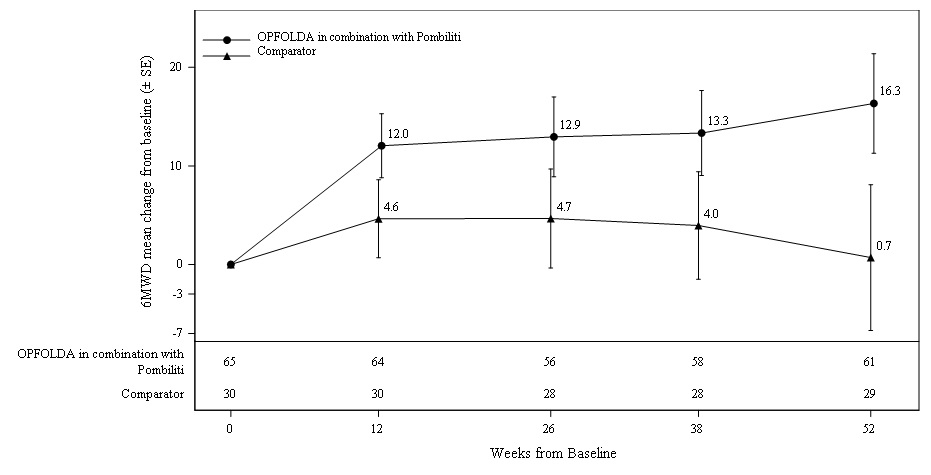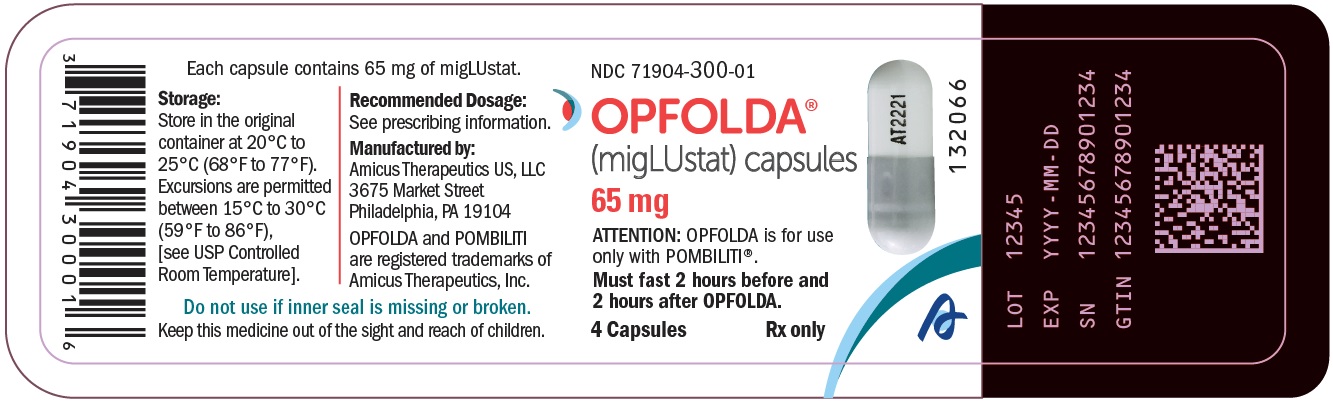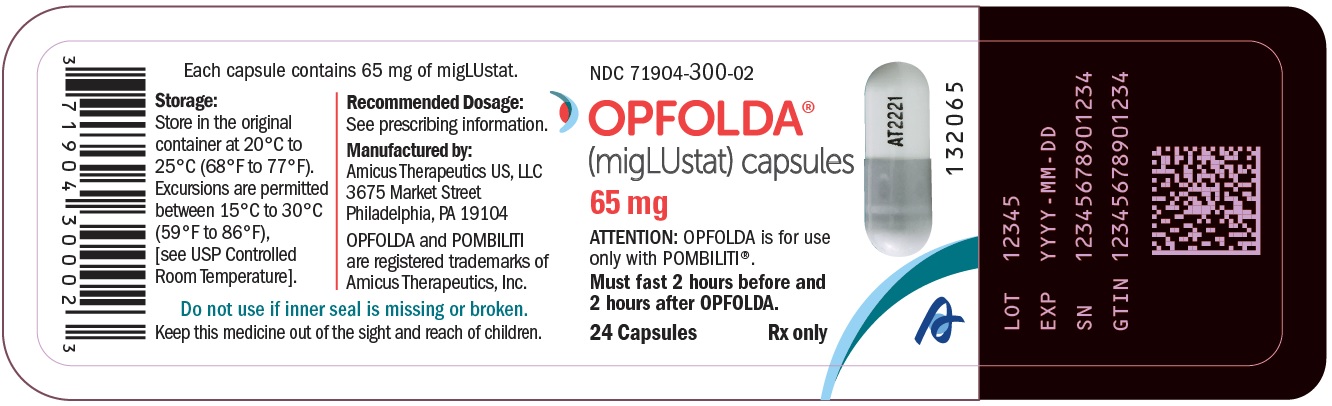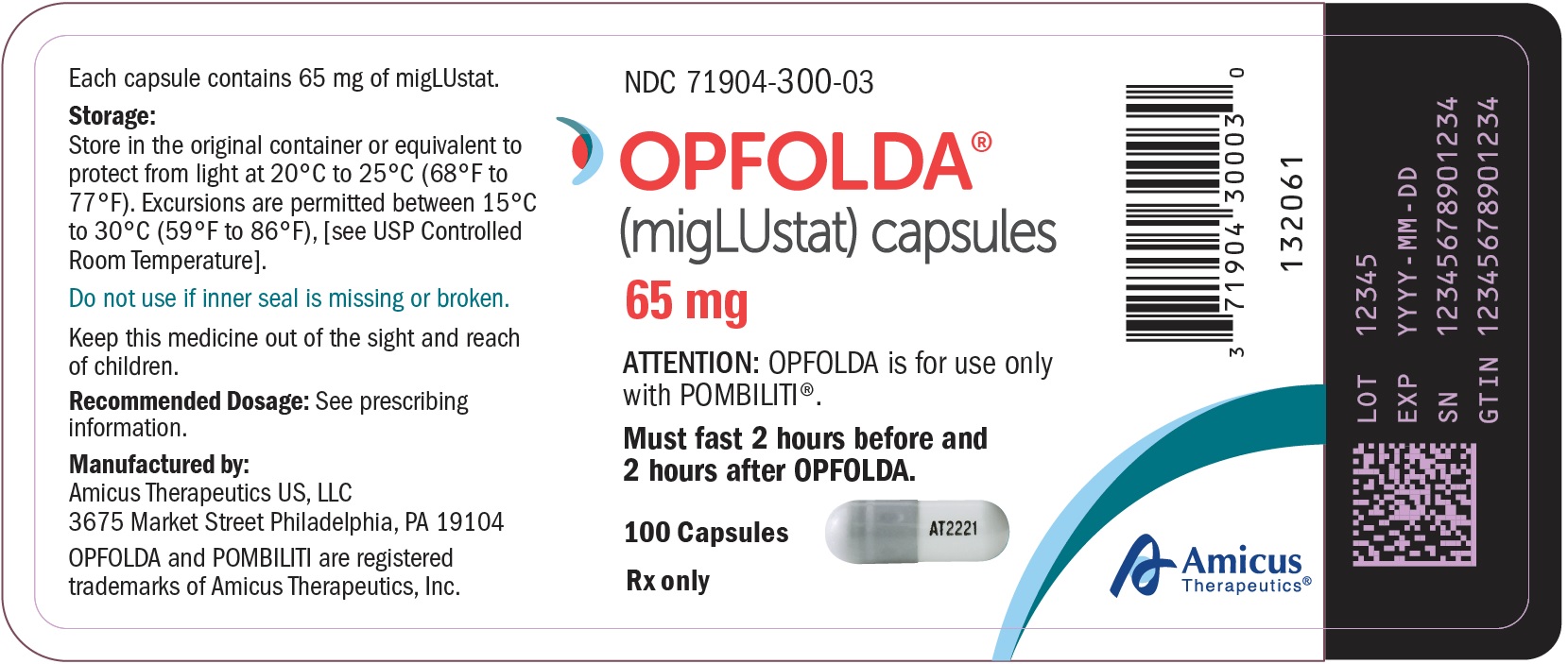 DRUG LABEL: OPFOLDA
NDC: 71904-300 | Form: CAPSULE
Manufacturer: AMICUS THERAPEUTICS US, LLC
Category: prescription | Type: HUMAN PRESCRIPTION DRUG LABEL
Date: 20241127

ACTIVE INGREDIENTS: MIGLUSTAT 65 mg/1 1

HIGHLIGHTS OF PRESCRIBING INFORMATION

These highlights do not include all the information needed to use OPFOLDA® safely and effectively. See full prescribing information for OPFOLDA.
OPFOLDA (miglustat) capsules, for oral use
Initial U.S. Approval: 2003

1 INDICATIONS AND USAGE

OPFOLDA is an enzyme stabilizer indicated, in combination with Pombiliti, a hydrolytic lysosomal glycogen-specific enzyme, for the treatment of adult patients with late-onset Pompe disease (lysosomal acid alpha-glucosidase [GAA] deficiency) weighing ≥40 kg and who are not improving on their current enzyme replacement therapy (ERT). (1)

2 DOSAGE AND ADMINISTRATION

- Verify pregnancy status in females of reproductive potential prior to initiating treatment. (2.1)
- Administer OPFOLDA in combination with Pombiliti. (2.2)
- Recommended OPFOLDA dosage (based on actual body weight), administered orally every other week, is: (2.2)
  - 260 mg for patients weighing ≥50 kg.
  - 195 mg for patients weighing ≥40 kg to <50 kg.
- Start OPFOLDA in combination with Pombiliti 2 weeks after the last ERT dose. (2.2)
- Take OPFOLDA with an unsweetened beverage approximately 1 hour before the start of Pombiliti infusion; do not consume other beverages or food for at least 2 hours prior to and 2 hours after taking OPFOLDA. (2.2)
- Missed dose: If the OPFOLDA dosage is missed, Pombiliti should not be administered and treatment should be rescheduled at least 24 hours after OPFOLDA was last taken. If OPFOLDA in combination with Pombiliti are both missed, re-start treatment as soon as possible. (2.2)
- See full prescribing information for recommended OPFOLDA dosage in patients with renal impairment. (2.3)

3 DOSAGE FORMS AND STRENGTHS

Capsules: 65 mg (3)

4 CONTRAINDICATIONS

Pregnancy. (4, 5.1, 8.1)

5 WARNINGS AND PRECAUTIONS

- Embryo-Fetal Toxicity: May cause embryo-fetal harm. Advise females of reproductive potential of the potential risk to a fetus and to use effective contraception during treatment and for at least 60 days after the last dose. (4, 5.1, 8.1, 8.3)
- Risks Associated with Pombiliti: Refer to the Pombiliti Prescribing Information for a description of additional risks for Pombiliti. (5.2)

6 ADVERSE REACTIONS

Most common adverse reactions ≥5% are headache, diarrhea, fatigue, nausea, abdominal pain, and pyrexia. (6.1)

To report SUSPECTED ADVERSE REACTIONS, contact Amicus Therapeutics at 1-877-4AMICUS or FDA at 1-800-FDA-1088 or www.fda.gov/medwatch.

8 USE IN SPECIFIC POPULATIONS

- Lactation: Breastfeeding not recommended. (8.2)

FULL PRESCRIBING INFORMATION

1 INDICATIONS AND USAGE

OPFOLDA is indicated, in combination with Pombiliti, for the treatment of adult patients with late-onset Pompe disease (lysosomal acid alpha-glucosidase [GAA] deficiency) weighing ≥40 kg and who are not improving on their current enzyme replacement therapy (ERT).

2 DOSAGE AND ADMINISTRATION

2.1 Pregnancy Evaluation Prior to Initiating Treatment

Verify the pregnancy status of females of reproductive potential prior to initiating OPFOLDA in combination with Pombiliti [see Use in Specific Populations (8.1, 8.3)].

2.2 Recommended Dosage and Administration

OPFOLDA must be administered in combination with Pombiliti (see Figure 1 for the dosing timeline). Refer to the Pombiliti Prescribing Information for Pombiliti dosage and administration recommendations.

The recommended dosage of OPFOLDA is based on actual body weight. For patients weighing:

- ≥50 kg, the recommended dosage is 260 mg orally every other week.
- ≥40 kg to <50 kg, the recommended dosage is 195 mg orally every other week.

Start OPFOLDA in combination with Pombiliti 2 weeks after the last ERT dose. Take OPFOLDA approximately 1 hour before intravenous administration of Pombiliti. Swallow the OPFOLDA capsules whole only with unsweetened beverages (e.g., water, tea or coffee with no cream, sugar, or sweeteners). Do not consume other beverages or food for at least 2 hours prior to and 2 hours after administration of OPFOLDA.

Missed Dose
If the OPFOLDA dosage is missed, Pombiliti should not be administered and treatment should be rescheduled at least 24 hours after OPFOLDA was last taken. If OPFOLDA in combination with Pombiliti are both missed, re-start treatment as soon as possible.

Figure 1. Dosing Timeline

2.3 Recommended Dosage in Patients with Renal Impairment

The recommended dosage of OPFOLDA in patients with moderate or severe renal impairment is shown in Table 1 [see Clinical Pharmacology (12.3)].

Table 1. Recommended OPFOLDA Dosage in Patients with Moderate or Severe Renal Impairment

Patient Weight | Moderate Renal Impairment∗(CLcr 30-59 mL/minute) | Severe Renal Impairment∗ (CLcr 15-29 mL/minute)
≥50 kg | 195 mg | 195 mg
≥40 kg to <50 kg | 130 mg | 130 mg
∗ Renal function classified by CLcr (creatinine clearance) based on the Cockcroft-Gault equation.

For patients with mild renal impairment (creatinine clearance based on the Cockcroft-Gault equation, CLcr 60-89 mL/minute), the recommended OPFOLDA dosage is the same as for patients with normal renal function.

3 DOSAGE FORMS AND STRENGTHS

Capsules: 65 mg of miglustat, white opaque hard gelatin capsule with grey opaque cap with “AT2221” printed in black on the body.

4 CONTRAINDICATIONS

OPFOLDA in combination with Pombiliti is contraindicated in Pregnancy [see Use in Specific Populations (8.1)]

5 WARNINGS AND PRECAUTIONS

5.1 Embryo-Fetal Toxicity

Based on findings from animal reproduction studies, OPFOLDA in combination with Pombiliti may cause embryo-fetal harm when administered to a pregnant female and is contraindicated during pregnancy. In a rabbit embryo-fetal development study, great vessel and cardiac malformations were increased in offspring of pregnant rabbits treated with oral miglustat in combination with cipaglucosidase alfa-atga at 3-fold and 16-fold, respectively, the maximum recommended human dose (MRHD) based on plasma AUC exposure.

Verify the pregnancy status in females of reproductive potential prior to initiating treatment with OPFOLDA in combination with Pombiliti. Advise females of reproductive potential to use effective contraception during treatment with OPFOLDA in combination with Pombiliti and for at least 60 days after the last dose [see Use in Specific Populations (8.1, 8.3)].

5.2 Risks Associated with Pombiliti

OPFOLDA must be administered in combination with Pombiliti. Refer to the Pombiliti Prescribing Information for a description of additional risks for Pombiliti including, but not limited to, the warnings and precautions for Pombiliti.

6 ADVERSE REACTIONS

6.1 Clinical Trials Experience

Because clinical trials are conducted under widely varying conditions, adverse reaction rates observed in the clinical trials of a drug cannot be directly compared to rates in the clinical trials of another drug and may not reflect the rates observed in practice.

Adverse Reactions from the Pooled Clinical Trials Including Trial 1

The pooled safety analysis from 3 clinical trials included 151 adult patients with late-onset Pompe disease (LOPD) treated with OPFOLDA in combination with Pombiliti including:

- 85 patients in the randomized, double-blind, active-controlled trial in adults (Trial 1) [see Clinical Studies (14)],
- 37 patients in the open-label extension trial where patients switched from a non‑U.S.‑approved alglucosidase alfa product [see Clinical Studies (14)] to OPFOLDA in combination with Pombiliti,
- 29 patients in an open-label trial.

The total median duration of exposure in these trials was 21 months, with 120 patients having at least 12 months exposure to OPFOLDA in combination with Pombiliti. In these trials, 78% (n=117) of the patients received previous ERT (ERT‑experienced) with a mean treatment duration of 7.7 years.

The most common adverse reactions (≥5%) reported in the pooled safety population of patients treated with OPFOLDA in combination with Pombiliti in the 3 clinical trials were headache, diarrhea, fatigue, nausea, abdominal pain, and pyrexia.

Adverse Reactions from Trial 1

Trial 1 (a randomized, double-blind, active-controlled trial) included 123 adult patients with LOPD who were randomized in a 2:1 ratio to receive treatment with OPFOLDA in combination with Pombiliti or a non-U.S.-approved alglucosidase alfa product with placebo [see Clinical Studies (14)].

The duration of exposure was similar for both treatment groups (overall mean exposure of 12 months). Most patients (77%) were ERT‑experienced, and a majority of patients in both treatment groups had >5 years of prior treatment with ERT (69% and 63% of patients in the OPFOLDA in combination with Pombiliti group and the non-U.S.-approved alglucosidase alfa product with placebo group, respectively).

The most common adverse reactions (≥5%) reported in the patients who received OPFOLDA in combination with Pombiliti in Trial 1 were headache and diarrhea.

Table 2 summarizes frequent adverse reactions that occurred in patients treated with OPFOLDA in combination with Pombiliti in Trial 1. Trial 1 was not designed to demonstrate a statistically significant difference in the incidence of adverse reactions in the OPFOLDA in combination with Pombiliti and the non-U.S.-approved alglucosidase alfa product with placebo groups.

Table 2. Adverse Reactions that Occurred in Adults with LOPD at an Incidence of ≥2% in Trial 1

Adverse Reaction | OPFOLDA in Combination with Pombiliti (n=85) N (%) | A Non-U.S.-Approved Alglucosidase alfa Product with Placebo (n=38) N (%)
Headache∗ | 7 (8.2) | 3 (7.9)
Diarrhea | 5 (5.9) | 2 (5.3)
Dizziness | 4 (4.7) | 2 (5.3)
Dyspnea | 3 (3.5) | 0
Abdominal distention | 3 (3.5) | 2 (5.3)
Pyrexia | 3 (3.5) | 1 (2.6)
Rash† | 3 (3.5) | 0
Abdominal pain‡ | 2 (2.4) | 4 (10.5)
Nausea | 2 (2.4) | 5 (13.2)
Chills | 2 (2.4) | 0
Dysgeusia | 2 (2.4) | 0
Flushing | 2 (2.4) | 0
Muscle spasms | 2 (2.4) | 0
Pruritus | 2 (2.4) | 2 (5.3)
Tachycardia§ | 2 (2.4) | 0
Urticaria¶ | 2 (2.4) | 0
LOPD: late-onset Pompe disease
∗ Headache included migraine and migraine with aura.
† Rash included erythematous rash and macular rash.
‡ Abdominal pain included upper and lower abdominal pain.
§ Tachycardia included sinus tachycardia.
¶ Urticaria included mechanical urticaria and urticarial rash.

Additional adverse reactions reported in at least 2% of patients treated with OPFOLDA in combination with Pombiliti across the 3 clinical trials include: myalgia, arthralgia, increased blood pressure, pain, tremor, dyspepsia, asthenia, constipation, infusion site swelling, flank pain, malaise, paresthesia, somnolence, and decreased platelet count.

8 USE IN SPECIFIC POPULATIONS

8.1 Pregnancy

Risk Summary

Based on findings from animal reproduction studies, OPFOLDA in combination with Pombiliti may cause embryo-fetal harm when administered to a pregnant female and is contraindicated during pregnancy. In a rabbit embryo-fetal development study, great vessel and cardiac malformations were increased in offspring of pregnant rabbits treated with miglustat in combination with cipaglucosidase alfa-atga at 3-fold and 16-fold, respectively, the MRHD of OPFOLDA and Pombiliti based on plasma AUC exposure. A No Observed Adverse Effect Level (NOAEL) was not identified for the combination. In a pre- and post-natal development study in rats, increases in pup mortality were seen following maternal treatment with miglustat in combination with cipaglucosidase alfa-atga (400 mg/kg), or with cipaglucosidase alfa-atga (400 mg/kg) alone. The NOAEL for cipaglucosidase alfa-atga alone is 150 mg/kg (5-fold the Pombiliti MRHD margin). A NOAEL for the combination was not identified. Margins at the lowest observed adverse effect level (LOAEL), relative to exposures at the MRHD of OPFOLDA and Pombiliti were 4-fold and 20-fold, respectively, based on plasma AUC exposure (see Data).

There are no available human data on OPFOLDA in combination with Pombiliti use in pregnant females to evaluate for a drug-associated risk of major birth defects, miscarriage, or other adverse maternal or fetal outcomes.

Data

Animal Data
Reproductive toxicity studies of cipaglucosidase alfa-atga in rats and rabbits included pretreatment with diphenhydramine (DPH) to prevent or minimize hypersensitivity reactions.

In a rabbit embryo-fetal development study, 25 mg/kg oral miglustat alone, or in combination with intravenous cipaglucosidase alfa-atga 175 mg/kg, was administered every other day to pregnant females during organogenesis (Gestation Day [GD] 7 through GD 19). Additional experimental groups received cipaglucosidase alfa-atga (30, 70, or 175 mg/kg) with the same dosing frequency during organogenesis. Clusters of great vessel and cardiac malformations were increased in offspring of pregnant rabbits treated with the combination of miglustat and cipaglucosidase alfa-atga at 3-fold and 16-fold the MRHD of OPFOLDA and Pombiliti, respectively, based on plasma AUC exposure. A NOAEL for the combination was not identified. One fetus treated with miglustat alone (25 mg/kg) and one fetus treated with cipaglucosidase alfa-atga alone (175 mg/kg), each showed a similar cluster of these great vessel and cardiac malformations.

In a rat embryo-fetal development study, 60 mg/kg oral miglustat alone, or in combination with intravenous cipaglucosidase alfa-atga 400 mg/kg, was administered every other day to pregnant rats during organogenesis (GD 6 through GD 18). Additional experimental groups received cipaglucosidase alfa-atga (75, 150, or 400 mg/kg) with the same dosing frequency during organogenesis. No evidence of adverse effects was noted in pregnant rats or their offspring in any experimental group. The margin at the NOAEL for miglustat (60 mg/kg) was 4-fold the OPFOLDA MRHD based on plasma AUC exposure. The margin at the NOAEL for cipaglucosidase alfa-atga (400 mg/kg) was 20-fold the Pombiliti MRHD based on plasma AUC exposure.

In a pre-and post-natal development study in rats, 60 mg/kg oral miglustat alone, or in combination with intravenous cipaglucosidase alfa-atga 400 mg/kg, was administered to pregnant females every other day from GD 6 through GD 18, and from Lactation Day (LD) 1 through LD 19. Additional experimental groups received cipaglucosidase alfa-atga (75, 150, or 400 mg/kg) with the same dosing frequency during pregnancy and lactation. Maternal and pup mortality were increased with the combination, and pup mortality was also increased with cipaglucosidase alfa-atga 400 mg/kg alone. The NOAEL for cipaglucosidase alfa-atga alone is 150 mg/kg (5-fold the Pombiliti MRHD margin). A NOAEL was not identified for the combination, for which LOAEL margins at the MRHD of OPFOLDA and Pombiliti were 4-fold and 20-fold, respectively, based on plasma AUC exposure.

8.2 Lactation

Risk Summary

There are no data on the presence of miglustat, alone or in combination with cipaglucosidase alfa-atga, in human milk, the effects on the breastfed infant, or the effects on milk production. Miglustat is present in animal milk (see Data). When a drug is present in animal milk, it is likely that the drug will be present in human milk. Based on findings in animal studies, the use of OPFOLDA in combination with Pombiliti may lead to serious adverse reactions in breastfed infants. Advise females that breastfeeding is not recommended while on treatment with OPFOLDA in combination with Pombiliti.

Data

Evaluation of milk in rats from the pre- and post-natal development study of miglustat in combination with cipaglucosidase alfa-atga (60 mg/kg and 400 mg/kg, respectively) showed secretion of miglustat and excretion of cipaglucosidase alfa-atga in rat milk. In this study, the ratio of miglustat exposure in rat milk to the miglustat exposure in rat plasma was 1.7, and the ratio of cipaglucosidase alfa-atga exposure in rat milk to the cipaglucosidase alfa-atga exposure in rat plasma was <4%.

The concentration of drug in animal milk does not necessarily predict the concentration of drug in human milk.

8.3 Females and Males of Reproductive Potential

OPFOLDA in combination with Pombiliti may cause embryo-fetal harm when administered to a pregnant female [see Use in Specific Populations (8.1)].

Pregnancy Testing

Verify the pregnancy status in females of reproductive potential prior to initiating treatment with OPFOLDA in combination with Pombiliti.

Contraception

Females
Advise females of reproductive potential to use effective contraception during treatment with OPFOLDA in combination with Pombiliti and for at least 60 days after the last dose.

Infertility

Females
Based on preimplantation loss observed in female rats treated with oral miglustat (60 mg/kg) in combination with intravenous cipaglucosidase alfa-atga (400 mg/kg) every other day for 14 days prior to mating and continuing through GD 7, OPFOLDA in combination with Pombiliti may impair human female fertility. A NOAEL for the combination was not identified. The LOAEL margins are 4-fold and 27-fold the MRHD for OPFOLDA and Pombiliti, respectively. It is not known whether this preimplantation loss in female rats would be sustained if dosing with the combination were discontinued prior to mating [see Nonclinical Toxicology (13.1)].

Males
Based on reversible increases in preimplantation loss in male rats treated with the combination every other day for 28 days prior to mating, OPFOLDA in combination with Pombiliti may impair human male fertility. A NOAEL for the combination was not identified. The LOAEL margins are 4-fold and 27-fold the MRHD for OPFOLDA and Pombiliti, respectively [see Nonclinical Toxicology (13.1)].

For additional information about male fertility with the use of Pombiliti, see the Pombiliti Prescribing Information.

8.4 Pediatric Use

Safety and effectiveness of OPFOLDA in combination with Pombiliti have not been established in pediatric patients with late-onset Pompe disease.

8.5 Geriatric Use

Of the total number of patients treated with OPFOLDA in combination with Pombiliti in clinical trials for LOPD, 17 (11%) were 65 to 74 years of age, and none were 75 years of age and older [see Clinical Studies (14)].

Clinical trials of OPFOLDA in combination with Pombiliti did not include sufficient numbers of patients 65 years of age and older to determine whether they respond differently from younger adult patients.

8.6 Renal Impairment

Plasma concentrations of miglustat increased in patients with renal impairment [see Clinical Pharmacology (12.3)]. No dosage adjustment of OPFOLDA is recommended in patients with mild (CLcr 60 to 89 mL/minute, estimated by Cockcroft-Gault) renal impairment. Reduce the OPFOLDA dosage in patients with moderate (CLcr 30 to 59 mL/minute) or severe (CLcr 15 to 29 mL/minute) renal impairment [see Dosage and Administration (2.3)]. The pharmacokinetics of miglustat have not been evaluated in patients with end stage renal disease.

11 DESCRIPTION

Miglustat is an N-alkylated iminosugar, a synthetic analog of D‑glucose. The pharmacologic class is enzyme stabilizer.

The chemical name is 1,5-(butylimino)-1,5-dideoxy-D-glucitol with the molecular weight of 219.28 g/mol, the molecular formula C10H21NO4, and the following chemical structure:

Miglustat is a white to off-white crystalline solid (powder). It is highly soluble in water (>1,000 mg/mL as a free base).

OPFOLDA (miglustat) capsules each contain 65 mg of miglustat for oral administration. The inactive ingredients are: colloidal silicon dioxide, magnesium stearate, microcrystalline cellulose, pregelatinized maize starch, and sucralose. The capsule shells include black iron oxide, gelatin, and titanium dioxide. Edible printing ink includes black iron oxide, and shellac.

12 CLINICAL PHARMACOLOGY

12.1 Mechanism of Action

Miglustat binds with, stabilizes, and reduces inactivation of cipaglucosidase alfa-atga in the blood after infusion. The bound miglustat is dissociated from cipaglucosidase alfa-atga after it is internalized and transported into lysosomes. Miglustat alone has no pharmacological activity in cleaving glycogen.

12.2 Pharmacodynamics

The exposure-response relationship and time course of pharmacodynamic response for the safety and effectiveness of miglustat have not been fully characterized.

12.3 Pharmacokinetics

Miglustat maximum concentration (Cmax) and area under the plasma concentration-time curve (AUC) increases proportionally over a dosage range from 130 mg to 260 mg (0.5 to 1 times the approved recommended dosage of 260 mg in patients weighing ≥50 kg). At the recommended 260 mg dose, the mean (SD) Cmax was approximately 3 (0.9) mcg/mL and the mean AUC was approximately 25 (6.5) mcg∗hr/mL.

Absorption
The mean time to reach the maximum concentration (Tmax) of miglustat ranged from 2 hours to 3 hours.

Effect of Food
Co-administration of miglustat with food is predicted to result in delayed absorption and decreased Cmax in healthy subjects [see Dosage and Administration (2.2)].

Distribution
The apparent volume of distribution of miglustat was approximately 94 L in adult patients with LOPD.

Elimination
The apparent clearance of miglustat was approximately 10 L/hr. The terminal elimination half‑life was approximately 6 hours.

Specific Populations
No clinically significant differences in the pharmacokinetics of miglustat were observed based on age (18 to 74 years) and sex. The effect of hepatic impairment on the pharmacokinetics of miglustat is unknown.

Patients with Renal Impairment
The AUC0-24hr of miglustat increased by 21%, 32%, and 41% in patients with mild (CLcr 60 to 89 mL/minute, estimated by Cockcroft-Gault), moderate (CLcr 30 to 59 mL/minute), and severe (CLcr 15 to 29 mL/minute) renal impairment, respectively, compared to patients with normal renal function. The effect of end stage renal disease on the pharmacokinetics of miglustat is unknown.

Drug Interaction Studies
In Vitro Studies
Cytochrome P450 (CYP) Enzymes: Miglustat is not a known substrate or inhibitor of CYP1A2, CYP2A6, CYP2C9, CYP2C19, CYP2D6, CYP2E1, CYP3A4, or CYP4A11.

Transporter Systems: Miglustat is a substrate of P-gp, OCT1, and OCT2 but not a substrate of OAT1, OAT3, OATP1B1, OATP1B3, MATE1, MATE2-K, BCRP, or BSEP. Miglustat is an inhibitor of MATE1, but is not an inhibitor of OAT1, OAT3, OCT1, OCT2, OATP1B1, OATP1B3, MATE2-K, P-gp, BCRP, or BSEP.

13 NONCLINICAL TOXICOLOGY

13.1 Carcinogenesis, Mutagenesis, Impairment of Fertility

Carcinogenesis
The carcinogenicity of OPFOLDA is based on studies from another miglustat product. Below are findings from the carcinogenicity studies with the other miglustat product.

Two-year carcinogenicity studies have been conducted with miglustat in CD-1 mice at oral doses up to 500 mg/kg/day and in Sprague Dawley rats at oral doses up to 180 mg/kg/day. Oral administration of miglustat for 104 weeks produced mucinous adenocarcinomas of the large intestine at 210, 420, and 500 mg/kg/day (about 3, 5, and 6-fold the MRHD of OPFOLDA 260 mg, respectively, based on body surface area [BSA]) in male mice and at 420 and 500 mg/kg/day (about 5 and 6-fold the MRHD of OPFOLDA 260 mg, respectively, based on BSA) in female mice. The adenocarcinomas were considered rare in CD-1 mice and occurred in the presence of inflammatory and hyperplastic lesions in the large intestine of both males and females. In rats, oral administration of miglustat for 100 weeks produced increased incidences of interstitial cell adenomas of the testis at 30, 60, and 180 mg/kg/day (about 1, 2, and 4-fold the MRHD of OPFOLDA 260 mg, respectively, based on BSA).

Mutagenesis
The mutagenicity of OPFOLDA is based on studies from another miglustat product. Below are findings from the carcinogenicity studies with the other miglustat product.

Miglustat was not mutagenic or clastogenic in a battery of in vitro and in vivo assays including the bacterial reverse mutation (Ames), chromosomal aberration (in human lymphocytes), gene mutation in mammalian cells (Chinese hamster ovary), and mouse micronucleus assays, in studies with another miglustat product.

Impairment of Fertility
In a fertility study in rats, oral miglustat (60 mg/kg) was administered alone, or in combination with intravenous cipaglucosidase alfa-atga (400 mg/kg), to male and female rats every other day. Dosing in males was initiated 28 days prior to cohabitation with untreated females. Dosing in females was initiated 14 days prior to cohabitation with untreated males and continued through GD 7. Additional experimental groups received intravenous cipaglucosidase alfa-atga alone (75, 150, or 400 mg/kg/day) with the same frequency over the same pre-mating interval (males) or pre-mating and pregnancy interval (females).

There was no effect on male or female rat fertility in any experimental group. Treatment of male rats with the combination was associated with increased preimplantation loss that was reversible. Treatment of female rats with the combination, or with miglustat alone, resulted in preimplantation loss; whether this would be reversible if treatment were discontinued prior to cohabitation is unknown. NOAELs were not identified for the combination in either male or female rats. The LOAEL margins for these doses represent 4-fold and 27-fold the MRHD of OPFOLDA and Pombiliti, respectively, based on plasma AUC exposures.

The impact of OPFOLDA on fertility is based, in part, on studies from another miglustat product. Below are findings from the fertility studies with the other miglustat product.

Fertility studies conducted with another miglustat product showed that male rats, given 20 mg/kg/day miglustat (exposure less than that expected for the MRHD of OPFOLDA 260 mg, based on BSA comparisons, mg/m^2) by oral gavage, 14 days prior to mating, had decreased spermatogenesis with altered sperm morphology and motility and decreased fertility. Decreased spermatogenesis was reversible following 6 weeks of miglustat withdrawal in this study. A higher dose of 60 mg/kg/day (2 times the MRHD of OPFOLDA, based on BSA comparisons, mg/m^2) resulted in seminiferous tubule and testicular atrophy/degeneration. Female rats were given oral miglustat gavage doses of 20, 60, and 180 mg/kg/day beginning 14 days before mating and continuing through gestation in this study. Effects observed at 20 mg/kg/day (systemic exposure less than the human therapeutic systemic exposure, based on BSA comparisons) included decreased corpora lutea, increased post-implantation loss, and decreased live births.

13.2 Animal Toxicology and/or Pharmacology

Animal toxicology findings of OPFOLDA are based, in part, from studies from another miglustat product. In studies conducted for this other miglustat product, the following effects were noted following daily administration.

In a 52-week monkey toxicity study of oral miglustat (750 and 2,000 mg/kg/day), histopathology findings in the absence of clinical signs in the central nervous system (brain, spine) including vascular mineralization and mineralization and necrosis of white matter were observed at both ≥750 and 2000 mg/kg/day. In a 4-week rat study of miglustat by oral gavage (180, 840, and 4200 mg/kg/day), vacuolization of white matter was observed at ≥180 mg/kg/day (5 times the MRHD of OPFOLDA 260 mg, based on BSA comparisons, mg/m^2). Vacuolization can sometimes occur as an artifact of tissue processing. In a 4-week dog toxicity study of miglustat by oral gavage (35, 70, 105, and 140 mg/kg/day), findings included tremor and absent corneal reflexes at 105 mg/kg/day (9 times the MRHD of OPFOLDA 260 mg, based on BSA comparisons, mg/m^2). In a 2-week rat toxicity study of miglustat by oral gavage (85, 165, 495, and 825 mg/kg/day), ataxia, diminished/absent pupillary, palpebral, or patellar reflexes were observed at ≥495 mg/kg/day (43 times the MRHD of OPFOLDA 260 mg, based on BSA comparisons, mg/m^2). In a 52-week rat toxicity study of miglustat by oral gavage (180, 420, 840, and 1,680 mg/kg/day), cataracts were observed at ≥180 mg/kg/day.

In a 2-week dog toxicity study of oral miglustat (85, 165, 495, and 825 mg/kg/day), gastrointestinal necrosis, inflammation, and hemorrhage were observed at ≥85 mg/kg/day (8 times the MRHD of OPFOLDA 260 mg based on BSA comparisons, mg/m^2). In a 26-week rat toxicity study of miglustat by oral gavage (300, 600, and 1,200 mg/kg/day), similar GI toxicity occurred at 1200 mg/kg/day. In a 52-week monkey toxicity study of miglustat by oral gavage (750 and 2,000 mg/kg/day), similar GI toxicity occurred at ≥750 mg/kg/day.

14 CLINICAL STUDIES

Trial 1 was a randomized, double‑blind, active‑controlled, international, multi-center clinical trial (NCT#03729362) in patients ≥18 years old diagnosed with LOPD. Patients were randomized 2:1 to receive OPFOLDA (260 mg orally for those ≥50 kg or 195 mg orally for those ≥40 kg to <50 kg) in combination with Pombiliti (20 mg/kg by intravenous infusion) or a non-U.S.-approved alglucosidase alfa product with placebo every other week for 52 weeks. The efficacy population included a total of 123 patients of whom 95 (77%) had received prior treatment with U.S.-approved alglucosidase alfa or a non-U.S.-approved alglucosidase alfa product (ERT‑experienced) and 28 (23%) were ERT‑naïve. More than two thirds (n=64, 67%) of ERT‑experienced patients had been on ERT treatment for more than 5 years prior to entering Trial 1 (mean of 7.4 years).

Demographics, baseline sitting forced vital capacity (FVC) (% predicted), and 6-minute walk distance (6MWD) were generally similar between the 2 treatment groups (see Table 5 for baseline sitting FVC [percent predicted] values). Of the 123 randomized patients, 56 were males, baseline mean age was 47 years old (range from 19 to 74 years old), and mean age at diagnosis was 39 years old (range from 1 to 66). The racial groups for the patients consisted of 104 White (85%), 6 Japanese (5%), 6 Other racial group (5%), 4 Asian (3%), 1 Native Hawaiian or other Pacific Islander (1%), 1 American Indian or Alaska Native (1%), and 1 Black or African American (1%).

Key efficacy endpoints included assessment of sitting FVC (% predicted) and 6MWD (Table 3 and Table 4).

Sitting FVC (Percent‑predicted) at 52 Weeks
Patients treated with OPFOLDA in combination with Pombiliti showed a mean change in sitting FVC from baseline at Week 52 of ‑1.1% as compared with patients treated with a non-U.S.-approved alglucosidase alfa product with placebo of ‑3.3%; the estimated treatment difference was 2.3% (95% CI: 0.02, 4.62).

The ERT‑experienced patients treated with OPFOLDA in combination with Pombiliti showed a numerically favorable change in sitting FVC from baseline at Week 52 (Table 3 and Figure 2).

Table 3. Summary of Sitting FVC in Adults with LOPD by ERT Status at 52 Weeks in Trial 1

Efficacy Endpoint | ERT-experienced |  | ERT-naïve*
Sitting FVC (% predicted) | OPFOLDA in Combination with Pombiliti | A Non-U.S.-Approved Alglucosidase alfa Product† with Placebo | OPFOLDA in Combination with Pombiliti | A Non-U.S.-Approved Alglucosidase alfa Product† with Placebo
Baseline n Mean (SD) Median | n=65 67.9 (19.1) 68.0 | n=30 67.5 (21.0) 69.0 | n=20 80.2 (18.7) 82.3 | n=8 79.6 (21.0) 88.5
Change from baseline at Week 52 n Mean (SD) Median | n=55 0.1 (5.9) 0.5 | n=26 -3.5 (4.7) -2.5 | n=19 -4.7 (6.2) -4.5 | n=7 -2.4 (6.3) -3.0
Change to Week 52 Diff. of means (SE) (95% CI) | 3.5 (1.3) (1.0, 6.0)‡ |  | -1.9 (2.7) (-7.3, 3.6)
FVC: forced vital capacity; LOPD: late-onset Pompe disease; ERT: enzyme replacement therapy; SD: standard deviation; Diff.: difference; SE: standard error; CI: confidence interval
∗ OPFOLDA in combination with Pombiliti is not approved for use in ERT-naïve patients with LOPD [see Indications and Usage (1)]. The ERT naïve patient subgroup enrolled too few patients to conclusively interpret the data. For the ERT-naïve group, the treatment difference was estimated using a 2-sample t-test.
† A U.S.-approved alglucosidase alfa product was not used in this clinical trial. Conclusions cannot be drawn from this clinical trial regarding comparative effectiveness between a U.S.-approved alglucosidase alfa product and OPFOLDA in combination with Pombiliti for the treatment of adult patients with LOPD weighing ≥40 kg and who are not improving on their current ERT.
‡ For the ERT-experienced group, the treatment difference of the mean was estimated by analysis of covariance which included treatment, gender, baseline FVC, age, weight, and height in the model. Nominal p=0.006. Missing data at Week 52 was imputed using last observed values.

Figure 2. Mean Change (± SE) in Sitting FVC (% predicted) from Baseline to Week 52 in ERT-experienced Adults with LOPD in Trial 1*

SE: standard error; FVC: forced vital capacity; ERT: enzyme replacement therapy; LOPD: late-onset Pompe disease
* A U.S.-approved alglucosidase alfa product was not used in this clinical trial. Conclusions cannot be drawn from this clinical trial regarding comparative effectiveness between a U.S.-approved alglucosidase alfa product and OPFOLDA in combination with Pombiliti for the treatment of adult patients with LOPD weighing ≥40 kg and who are not improving on their current ERT.

6-Minute Walk Distance (6MWD) at 52 Weeks
Patients treated with OPFOLDA in combination with Pombiliti walked on average 21 meters farther from baseline as compared to those treated with a non-U.S.-approved alglucosidase alfa product with placebo who walked 8 meters farther from baseline; the estimated treatment difference was 14 meters (95% CI: -1, 28).

The ERT-experienced patients treated with OPFOLDA in combination with Pombiliti showed a numerically favorable change in 6MWD from baseline at Week 52 (Table 4 and Figure 3).

Table 4. Summary of 6MWD in Adults with LOPD by ERT Status at 52 Weeks in Trial 1

Efficacy Endpoint | ERT-experienced |  | ERT-naïve*
6MWD | OPFOLDA in Combination with Pombiliti | A Non-U.S.-Approved Alglucosidase alfa Product† with Placebo | OPFOLDA in Combination with Pombiliti | A Non-U.S.-Approved Alglucosidase alfa Product† with Placebo
Baseline n Mean (SD) Median | n=65 347 (110) 353 | n=30 335 (114) 344 | n=20 394 (112) 375 | n=7 421 (136) 386
Change from baseline at Week 52 n Mean (SD) Median | n=61 16 (39) 10 | n=29 1 (40) -9 | n=20 33 (49) 24 | n=7 38 (29)) 34
Change to Week 52 Diff. of means (SE) (95% CI) | 17 (8) (0.2, 33)‡ |  | -5 (20) (-45, 36)
6MWD: 6-minute walk distance; LOPD: late-onset Pompe disease; ERT: enzyme replacement therapy; SD: standard deviation; Diff.: difference; SE: standard error; CI: confidence interval
∗ OPFOLDA in combination with Pombiliti is not approved for use in ERT-naïve patients with LOPD [see Indications and Usage (1)]. The ERT-naïve patient subgroup enrolled too few patients to conclusively interpret the data. For the ERT-naïve group, the treatment difference was estimated using a 2-sample t-test. One ERT-naïve subject in the control arm was excluded from this table because their change of 355 meters in 6MWD from baseline at Week 52 was a statistical outlier and not considered clinically plausible.
† A U.S.-approved alglucosidase alfa product was not used in this clinical trial. Conclusions cannot be drawn from this clinical trial regarding comparative effectiveness between a U.S.-approved alglucosidase alfa product and OPFOLDA in combination with Pombiliti for the treatment of adult patients with LOPD weighing ≥40 kg and who are not improving on their current ERT.
‡ For the ERT-experienced group, the treatment difference of the mean was estimated by nonparametric analysis of covariance which included treatment, gender, baseline 6MWD, age, weight, and height in the model. Nominal p=0.047. Missing data at Week 52 was imputed using last observed values.

Figure 3. Mean Change (± SE) of 6MWD from Baseline to Week 52 in ERT-experienced Adults with LOPD in Trial 1*

SE: standard error; 6MWD: 6-minute walk distance; ERT: enzyme replacement therapy; LOPD: late-onset Pompe disease
* A U.S.-approved alglucosidase alfa product was not used in this clinical trial. Conclusions cannot be drawn from this clinical trial regarding comparative effectiveness between a U.S.-approved alglucosidase alfa product and OPFOLDA in combination with Pombiliti for the treatment of adult patients with LOPD weighing ≥40 kg and who are not improving on their current ERT.

16 HOW SUPPLIED/STORAGE AND HANDLING

How Supplied
OPFOLDA (miglustat) capsules are supplied as 65 mg, white opaque hard gelatin capsules with a grey opaque cap with “AT2221” printed in black on the body, and are available in bottles with child resistant caps. See Table 5 for the available OPFOLDA packages.

Table 5. OPFOLDA Packages

Package Size | NDC
4 count bottle | 71904-300-01
24 count bottle | 71904-300-02
100 count bottle | 71904-300-03

Storage and Handling
Store at 20°C to 25°C (68°F to 77°F). Excursions are permitted between 15°C to 30°C (59°F to 86°F), [see USP Controlled Room Temperature].

Store in the original container to protect from light.

17 PATIENT COUNSELING INFORMATION

Advise the patient to read the FDA‑approved patient labeling (Patient Information).

OPFOLDA must be administered in combination with Pombiliti. Refer to the Pombiliti Prescribing Information for Pombiliti patient counseling information.

Administration
Advise the patient and caregiver to follow the timeline recommendations for taking OPFOLDA prior to the intravenous infusion with Pombiliti and to follow the fasting recommendation. Advise the patient and caregiver that OPFOLDA should be swallowed only with unsweetened beverages [see Dosage and Administration (2.2)].

Embryo-Fetal Toxicity
OPFOLDA in combination with Pombiliti may cause embryo-fetal harm. Advise a female patient and caregiver to inform their healthcare provider of a known or suspected pregnancy [see Warnings and Precautions (5.1) and Use in Specific Populations (8.1)].

Advise a female of reproductive potential to use effective contraception during treatment with OPFOLDA in combination with Pombiliti and for at least 60 days after the last dose [see Use in Specific Populations (8.1, 8.3)].

Lactation
Advise a lactating female not to breastfeed during treatment with OPFOLDA in combination with Pombiliti [see Use in Specific Populations (8.2)].

Infertility
Advise the male or female of reproductive potential that OPFOLDA in combination with Pombiliti may impair fertility [see Use in Specific Populations (8.3)].

Manufactured for:
Amicus Therapeutics US, LLC
3675 Market Street
Philadelphia, PA 19104

OPFOLDA and Pombiliti are registered trademarks of Amicus Therapeutics, Inc.
For more information, go to pombilitiopfoldahcp.com.

PATIENT INFORMATION

OPFOLDA® (op fol dah)
(miglustat)
capsules, for oral use

What is OPFOLDA?
OPFOLDA is a prescription medicine used in combination with Pombiliti for the treatment of adults with late-onset Pompe disease weighing 88 pounds (40 kg) or more and who are not improving on their current enzyme replacement therapy (ERT).

It is not known if OPFOLDA in combination with Pombiliti is safe and effective in children with late-onset Pompe disease.

Do not take OPFOLDA in combination with Pombiliti if you are pregnant. See “Before taking OPFOLDA, tell your healthcare provider about all of your medical conditions, including if you.”

Before taking OPFOLDA, tell your healthcare provider about all of your medical conditions, including if you:
have kidney problems
are pregnant or plan to become pregnant. OPFOLDA in combination with Pombiliti may cause harm to your unborn baby.
Females who are able to become pregnant:

- Your healthcare provider will check if you are pregnant before you start treatment with OPFOLDA in combination with Pombiliti.
- You should use effective birth control (contraception) during treatment with OPFOLDA in combination with Pombiliti and for at least 60 days after the last dose.
- Tell your healthcare provider right away if you become pregnant or think you might be pregnant during treatment with OPFOLDA in combination with Pombiliti.

are breastfeeding or plan to breastfeed. It is not known if OPFOLDA alone or in combination with Pombiliti passes into your breast milk. Do not breastfeed during treatment with OPFOLDA in combination with Pombiliti. Talk to your healthcare provider about the best way to feed your baby during this time.

Tell your healthcare provider about all the medicines you take, including prescription and over-the-counter medicines, vitamins, and herbal supplements.

How should I take OPFOLDA?
OPFOLDA must be taken in combination with Pombiliti. OPFOLDA in combination with Pombiliti will be given to you 1 time every other week.

Take OPFOLDA exactly as your healthcare provider tells you to.
Take your prescribed dose of OPFOLDA every other week about 1 hour before the start of your Pombiliti infusion.
Swallow OPFOLDA capsules whole only with unsweetened beverages, including water, tea or coffee with no cream, sugar, or sweeteners. Do not drink other beverages or eat food for at least 2 hours before
and 2 hours after taking OPFOLDA.
Your healthcare provider will stop your current ERT before starting your treatment with OPFOLDA in combination with Pombiliti.
If you miss a dose of OPFOLDA, you should not receive your Pombiliti infusion. Call your healthcare provider right away to reschedule your Pombiliti infusion.

What are the possible side effects of OPFOLDA in combination with Pombiliti?
The most common side effects of OPFOLDA in combination with Pombiliti include:
headache nausea
diarrhea stomach area pain
tiredness fever

OPFOLDA in combination with Pombiliti may cause fertility problems in females and males, which may affect the ability to have children. Talk to your healthcare provider if you have concerns about fertility.

These are not all of the possible side effects of OPFOLDA in combination with Pombiliti.

Call your doctor for medical advice about side effects. You may report side effects to FDA at 1-800-FDA-1088.

How should I store OPFOLDA?
Store OPFOLDA at room temperature between 68°F to 77°F (20°C to 25°C).
Keep OPFOLDA capsules in the original container to protect from light.

Keep OPFOLDA and all medicines out of the reach of children.

General information about the safe and effective use of OPFOLDA.

Medicines are sometimes prescribed for purposes other than those listed in a Patient Information leaflet. Do not use OPFOLDA for a condition for which it was not prescribed. Do not give OPFOLDA to other people, even if they have the same symptoms you have. It may harm them. You can ask your pharmacist or healthcare provider for information about OPFOLDA that is written for health professionals.

What are the ingredients in OPFOLDA?
Active ingredient: miglustat
Inactive ingredients: colloidal silicon dioxide, magnesium stearate, microcrystalline cellulose, pregelatinized maize starch, and sucralose. The capsule shell contains: black iron oxide, gelatin, and titanium dioxide. The edible printing ink contains: black iron oxide and shellac.

Manufactured for:
Amicus Therapeutics US, LLC
3675 Market Street
Philadelphia, PA 19104 USA
OPFOLDA and POMBILITI are registered trademarks of Amicus Therapeutics, Inc.
For more information, call AMICUS at 1-877-426-4287 or go to pombilitiopfolda.com.

This Patient Information has been approved by the U.S. Food and Drug Administration.

Issued: 7/2024